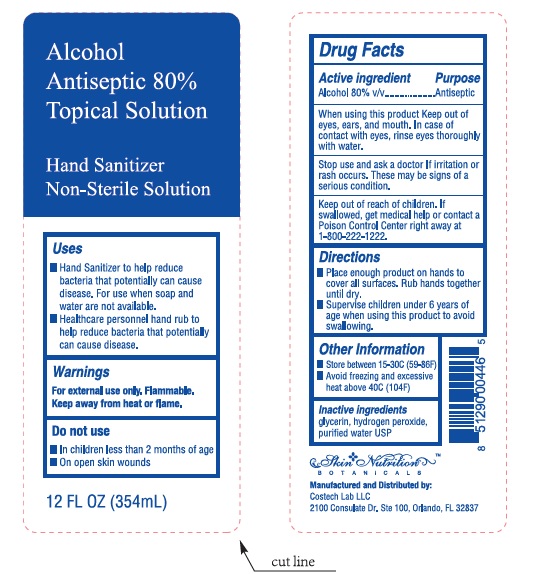 DRUG LABEL: Skin Nutritions
NDC: 80774-001 | Form: LIQUID
Manufacturer: Costech Lab LLC  Labaler
Category: otc | Type: HUMAN OTC DRUG LABEL
Date: 20200926

ACTIVE INGREDIENTS: ALCOHOL 80 mL/100 mL
INACTIVE INGREDIENTS: WATER; GLYCERIN; HYDROGEN PEROXIDE

Skin Nutritions

Active Ingredient

Alcohol 80%v/v

Purpose

Antiseptic

Warnings

- For external use only. Flammable. Keep away from heat or flame.
- Do not use . in children less than 2 months of age . on open skin wounds.
- When using this product keep out of eyes, ears, and mouth. In case of contact with eyes, rinse eyes thoroughly with water.
- Stop use and ask a doctor if irritation or rash occurs. These may be signs of a serious condition.

Uses

- Hand Sanitizer to help reduce bacteria that potentially can cause disease. For use when soap and water are not available.
- Health care personnel hand rub to help reduce bacteria that potentially can cause disease.

Directions

• Place enough product on hands to cover all surfaces. Rub hands together until dry.
• Supervise children under 6 years of age when using this product to avoid swallowing.

Keep out of reach of Children

- Store between 15-30C (59-86F)

• Avoid freezing and excessive heat above 40C (104F)

Inactive Ingredients

Glycerin, Hydrogen peroxide, Purified Water USP